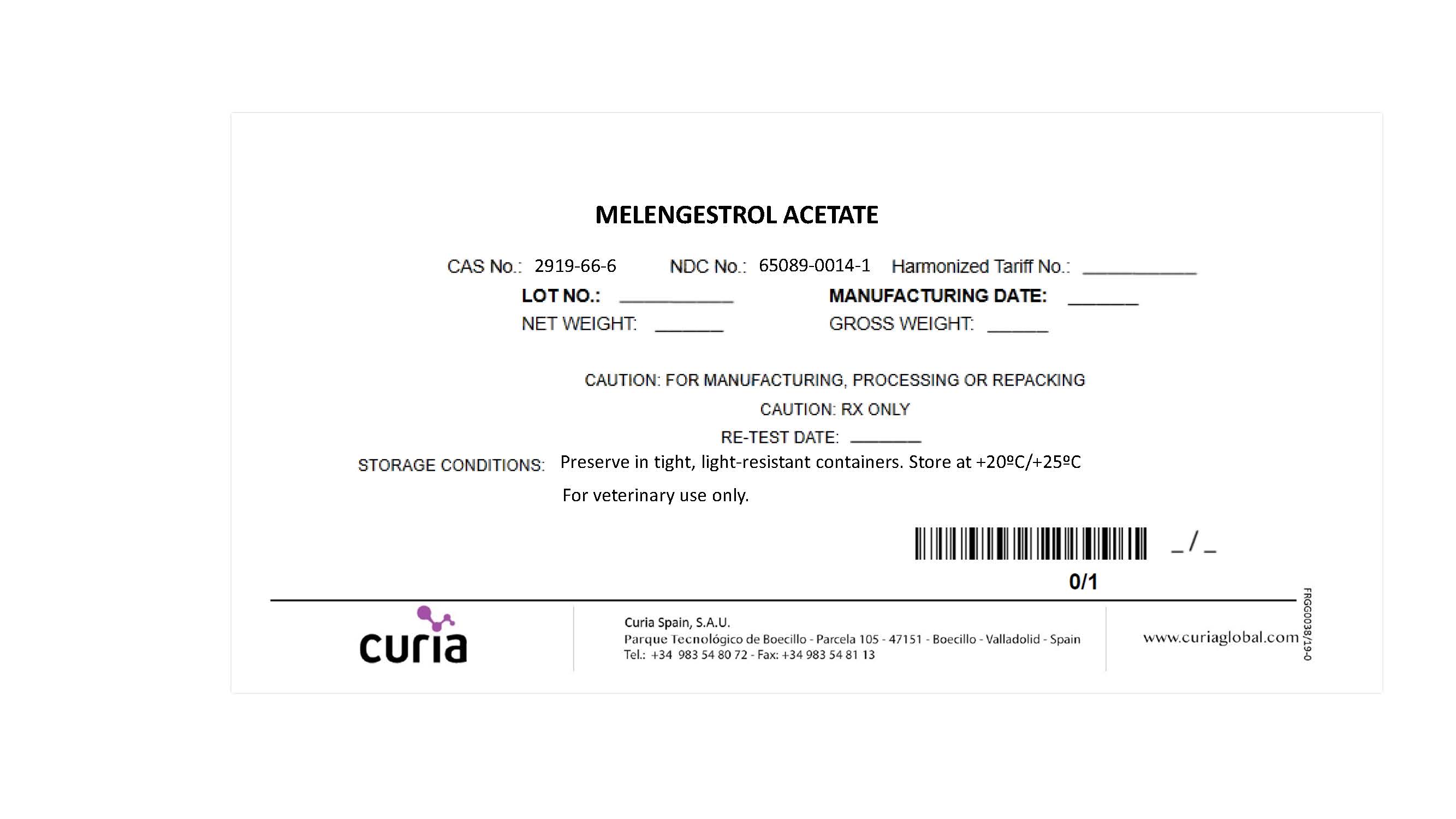 DRUG LABEL: Melengestrol acetate
NDC: 65089-0014 | Form: POWDER
Manufacturer: Curia Spain S.A.U.
Category: other | Type: BULK INGREDIENT
Date: 20211021

ACTIVE INGREDIENTS: MELENGESTROL ACETATE 1 kg/1 kg

Melengestrol acetate